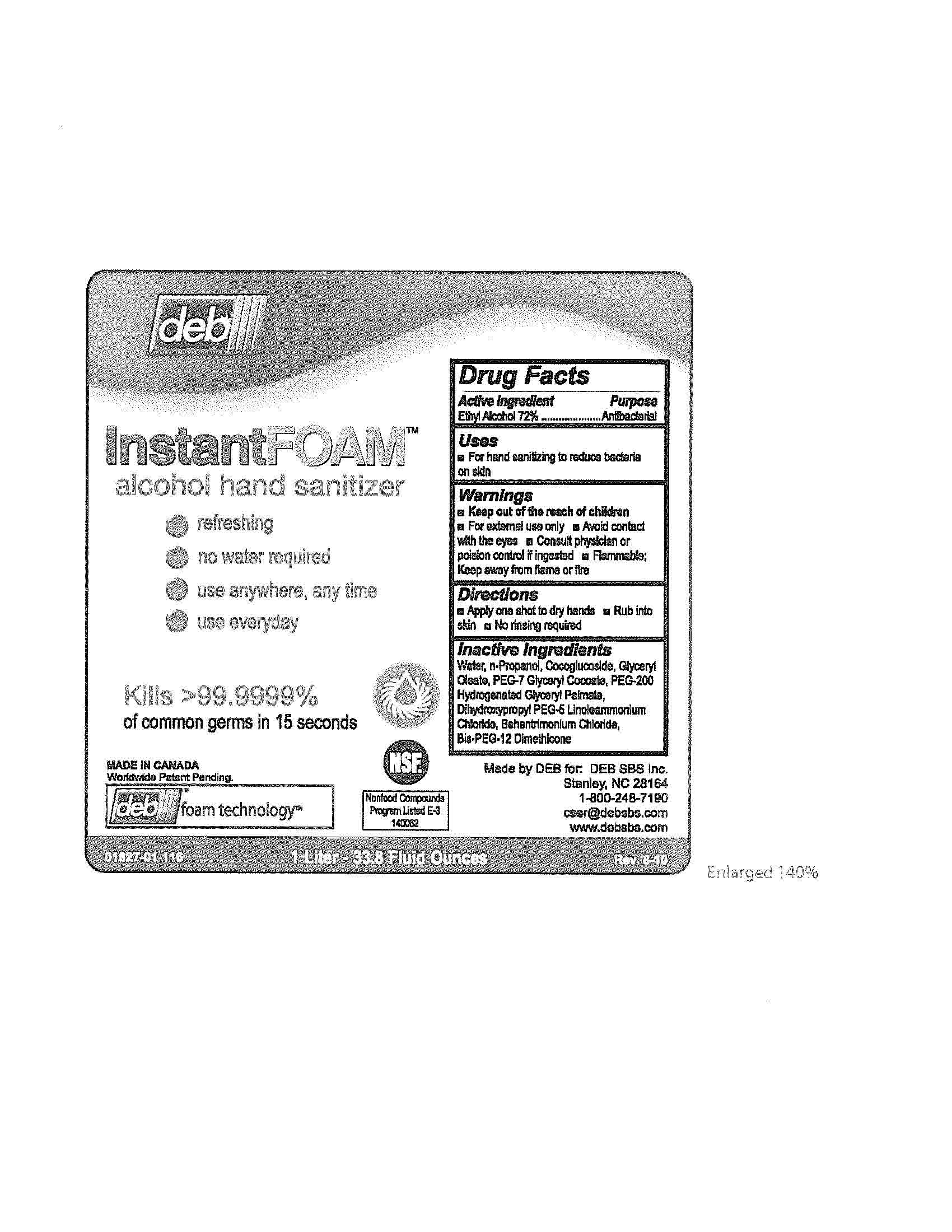 DRUG LABEL: InstantFOAM alcohol hand sanitizer
NDC: 11084-017 | Form: LIQUID
Manufacturer: Deb USA, Inc.
Category: otc | Type: HUMAN OTC DRUG LABEL
Date: 20100819

ACTIVE INGREDIENTS: Alcohol 72 mL/100 mL
INACTIVE INGREDIENTS: Water; DIHYDROXYPROPYL PEG-5 LINOLEAMMONIUM CHLORIDE; Propyl Alcohol; Behentrimonium Chloride

Drug Facts

Active Ingredient

Ethyl Alcohol 72%

Purpose
Antibacterial

Uses

For hand sanitizing to reduce bacteria on skin

Warnings

For external use only

Avoid contact with eyes

Flammable

Keep away from flame or fire

Keep out of reach of children.

Consult physician or poison control if ingested.

Directions

Apply one shot to dry hands

Rub into skin

No rinsing required

Inactive Ingredients

Water, n-Propanol, Cocoglucoside, Glyceryl Oleate, PEG-7 Glyceryl Cocoate, PEG-200 Hydrogenated Glyceryl Palmate, Dihydroxypropyl PEG-5 Linoleammonium Chloride, Behentrimonium Chloride, Bis-PEG-12 Dimethicone

PACKAGE LABEL

deb

Instant Foam

alcohol hand sanitizer

refreshing

no water required

use anywhere, any time

use everyday

Kills>99.9999%

of common germs in 15 seconds

Made in Canada

Worldwide Patent Pending

deb foam technology

NSF

Nonfood Compounds Program Listed E-3 140062

01827-01-116

1 Liter - 33.8 Fluid Ounces